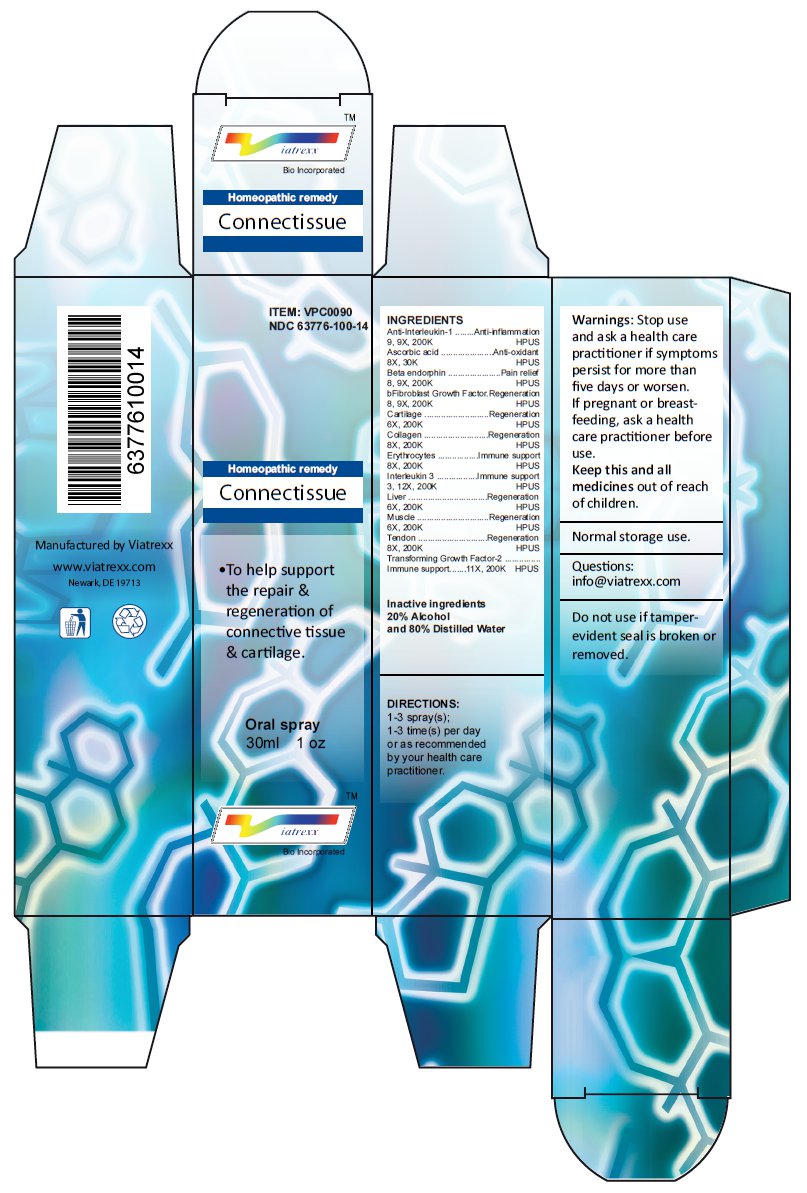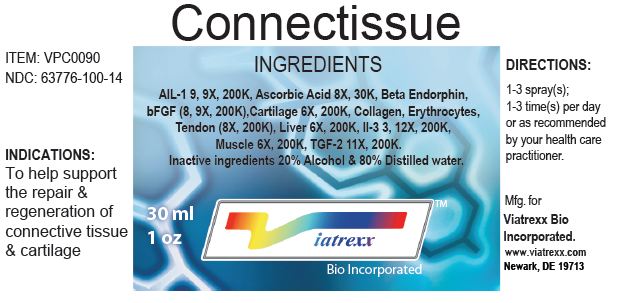 DRUG LABEL: Connectissue
NDC: 63776-100 | Form: SPRAY
Manufacturer: VIATREXX BIO INCORPORATED
Category: homeopathic | Type: HUMAN OTC DRUG LABEL
Date: 20221130

ACTIVE INGREDIENTS: SUS SCROFA TENDON 200 [kp_C]/1 mL; CETERMIN 200 [kp_C]/1 mL; ANTI-INTERLEUKIN-1.ALPHA. IMMUNOGLOBULIN G RABBIT 200 [kp_C]/1 mL; ASCORBIC ACID 30 [kp_C]/1 mL; METENKEFALIN 200 [kp_C]/1 mL; ERSOFERMIN 200 [kp_C]/1 mL; BOS TAURUS CARTILAGE 200 [kp_C]/1 mL; SUS SCROFA CARTILAGE 200 [kp_C]/1 mL; PORK COLLAGEN 200 [kp_C]/1 mL; BOS TAURUS RED BLOOD CELL 200 [kp_C]/1 mL; SUS SCROFA RED BLOOD CELL 200 [kp_C]/1 mL; INTERLEUKIN-3 200 [kp_C]/1 mL; BEEF LIVER 200 [kp_C]/1 mL; PORK LIVER 200 [kp_C]/1 mL; BEEF 200 [kp_C]/1 mL; PORK 200 [kp_C]/1 mL; BOS TAURUS TENDON 200 [kp_C]/1 mL
INACTIVE INGREDIENTS: ALCOHOL; WATER

Connectissue

Active Ingredients

Anti-Interleukin-1 9 9X 200K, Ascorbic acid 8X 30K, Beta endorphin 8 9X 200K, bFibroblast Growth Factor 8 9X 200K, Cartilage 6X 200K, Collagen 8X 200K, Erythrocytes 8X 200K, Interleukin 3 3 12X 200K, Liver 6X 200K, Muscle 6X 200K, Tendon 8X 200K, Transforming Growth Factor-2 11X 200K

Purpose

Anti-Interleukin-1 | Anti-inflammation
Ascorbic acid | Anti-oxidant
Beta endorphin | Pain relief
bFibroblast Growth Factor | Regeneration
Cartilage | Regeneration
Collagen | Regeneration
Erythrocytes | Immune support
Interleukin 3 | Immune support
Liver | Regeneration
Muscle | Regeneration
Tendon | Regeneration
Transforming Growth Factor-2 | Immune support

Uses

To help support the repair & regeneration of connective tissue & cartilage.

Warnings

Stop use and ask a health care practitioner if symptoms persist for more than five days or worsen. If pregnant or breastfeeding, ask a health care practitioner before use.

KEEP OUT OF REACH OF CHILDREN

Keep this and all medicines out of reach of children.

Directions

1-3 spray(s); 1-3 time(s) per day or as recommended by your health care practitioner.

Other Ingredients

Alcohol and Water

Other Information

Normal storage use.
Do not use if tamper-evident seal is broken or removed.

Principal Display Panel

ITEM: VPC0090
NDC 63776-100-14
Homeopathic remedy
Connectissue
• To help support the repair & regeneration of connective tissue & cartilage.
Oral spray
30ml 1 oz
Viatrexx™ Bio Incorporated
Manufactured by Viatrexx
www.viatrexx.com
Newark, DE 19713

Connectissue
30 mL
1 oz
Viatrexx™ Bio Incorporated
ITEM: VPC0090
NDC: 63776-100-14
INDICATIONS:
To help support the repair & regeneration of connective tissue & cartilage
DIRECTIONS:
1-3 spray(s); 1-3 time(s) per day or as recommended by your health care practitioner.
Mfg. for
Viatrexx Bio Incorporated.
www.viatrexx.com
Newark, DE 19713